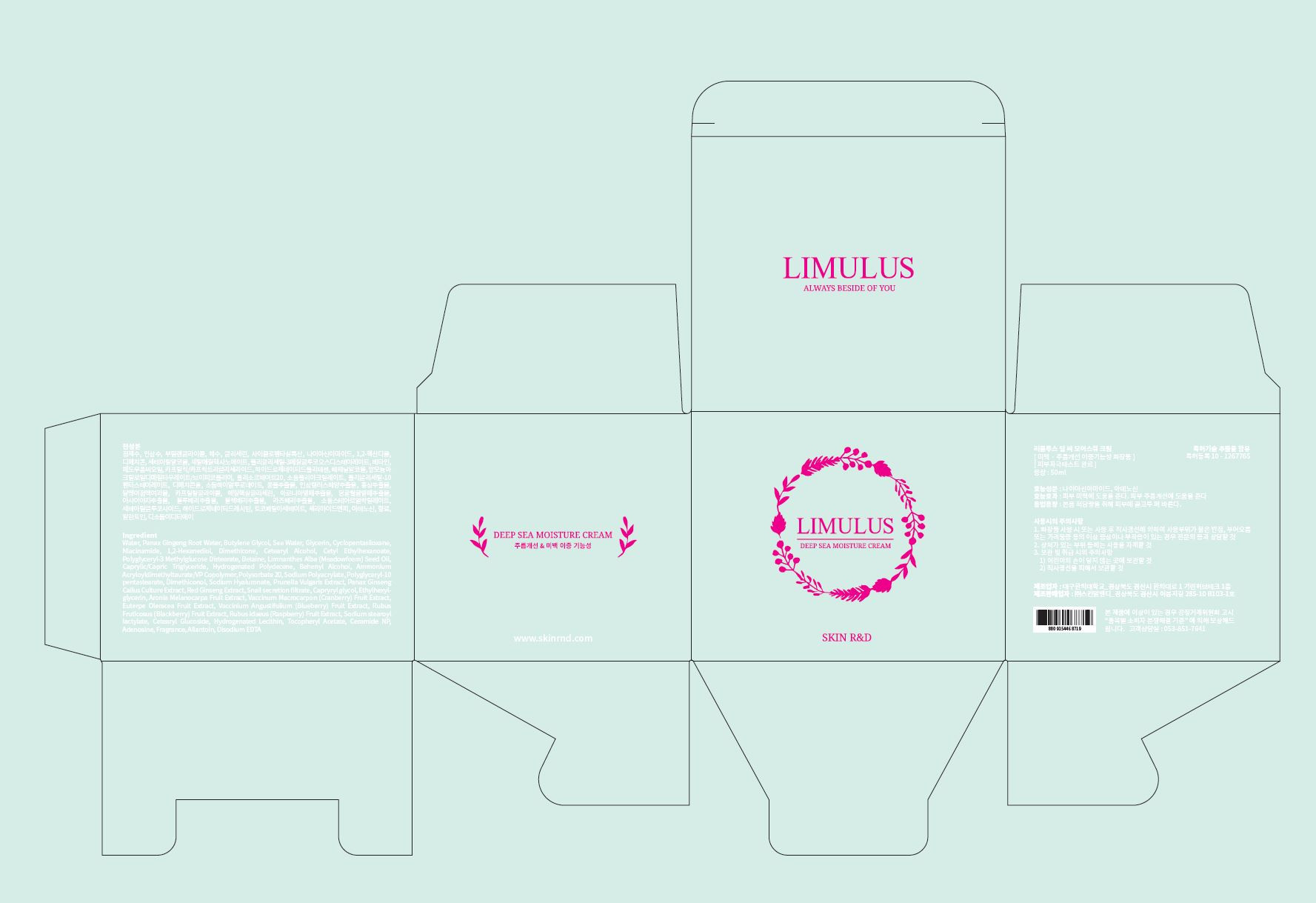 DRUG LABEL: Limulus Deep Sea Moisture
NDC: 71464-0001 | Form: CREAM
Manufacturer: Skin R&D
Category: otc | Type: HUMAN OTC DRUG LABEL
Date: 20170629

ACTIVE INGREDIENTS: ADENOSINE 0.04 g/100 mL; NIACINAMIDE 2 g/100 mL
INACTIVE INGREDIENTS: WATER; GLYCERIN

Drug Facts

ACTIVE INGREDIENT

niacinamide, adenosine

INACTIVE INGREDIENT

Water
Panax Ginseng Root Water
Glycerin
1,2-Hexanediol
Butylene Glycol
Sea Water
Butylene Glycol
Glycerin
Cyclopentasiloxane
Dimethicone
1,2-Hexanediol
Cetearyl Alcohol
Cetyl Ethylhexanoate
Polyglyceryl-3 Methylglucose Distearate
Behenyl Alcohol
Polyglyceryl-10 pentastearate
Sodium Stearoyl Lactylate
Betaine
Limnanthes Alba (Meadowfoam) Seed Oil
Caprylic/Capric Triglyceride
Hydrogenated Polydecene
Cyclopentasiloxane
Dimethiconol
Cetearyl Alcohol
Cetearyl Glucoside
Panax Ginseng Callus Extract
Water
Glycerin
Butylene Glycol
1,2-Hexanediol
Aronia Melanocarpa Fruit Extract
Glycerin
Butylene Glycol
Snail secretion filtrate
Butylene Glycol
Water
Butylene Glycol
Vaccinium Macrocarpon (Cranberry) Fruit Extract
Euterpe Oleracea Fruit Extract
Vaccinium Angustifolium (Blueberry) Fruit Extract
Rubus Fruticosus (Blackberry) Fruit Extract
Rubus Idaeus (Raspberry) Fruit Extract
Prunella Vulgaris Extract
Butylene Glycol
Ammonium Acryloyldimethyltaurate/VP Copolymer
Polysorbate 20
Sodium Polyacrylate
Fragrance
Allantoin
Caprylyl glycol
Ethylhexylglycerin
Hydrogenated Lecithin
Tocopheryl Acetate
Ceramide NP
Disodium EDTA
Red Ginseng Extract
Sodium Hyaluronate

PURPOSE

Skin brightening + Anti-wrinkle

keep out of reach of the children

INDICATIONS AND USAGE

Take an appropriate amount to the skin

WARNINGS

Precautions for Use

1. Consult with a medical specialist if any abnormal symptoms or side effects, such as red spots, swelling, or itching, occur during the use of this product.

2. Do not use the product on wounded areas.

3. Precautions for storage and handling

1) Keep out of reach of children.

2) Store away from direct sunlight.

DOSAGE AND ADMINISTRATION

for external use only